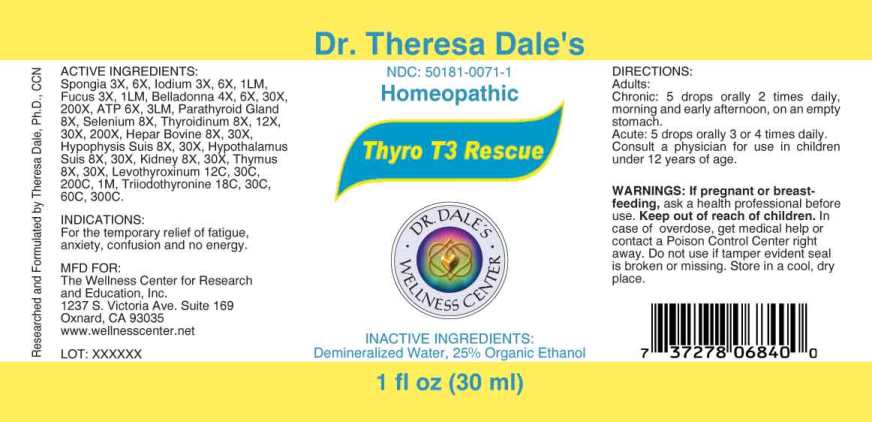 DRUG LABEL: Thyro T3 Rescue
NDC: 50181-0071 | Form: LIQUID
Manufacturer: The Wellness Center for Research and Education
Category: homeopathic | Type: HUMAN OTC DRUG LABEL
Date: 20250606

ACTIVE INGREDIENTS: SPONGIA OFFICINALIS SKELETON, ROASTED 3 [hp_X]/1 mL; IODINE 3 [hp_X]/1 mL; FUCUS VESICULOSUS 3 [hp_X]/1 mL; ATROPA BELLADONNA 4 [hp_X]/1 mL; ADENOSINE TRIPHOSPHATE DISODIUM 6 [hp_X]/1 mL; BOS TAURUS PARATHYROID GLAND 8 [hp_X]/1 mL; SELENIUM 8 [hp_X]/1 mL; THYROID 8 [hp_X]/1 mL; BEEF LIVER 8 [hp_X]/1 mL; SUS SCROFA PITUITARY GLAND 8 [hp_X]/1 mL; SUS SCROFA HYPOTHALAMUS 8 [hp_X]/1 mL; PORK KIDNEY 8 [hp_X]/1 mL; SUS SCROFA THYMUS 8 [hp_X]/1 mL; LEVOTHYROXINE 12 [hp_C]/1 mL; LIOTHYRONINE 18 [hp_C]/1 mL
INACTIVE INGREDIENTS: WATER; ALCOHOL

Drug Facts:

ACTIVE INGREDIENTS:

Spongia Tosta 3X, 6X, Iodium 3X, 6X, 1LM, Fucus Vesiculosus 3X, 1LM, Belladonna 4X, 6X, 30X, 200X, Adenosinum Triphosphoricum Dinatrum 6X, 3LM, Parathyroid Gland (Bovine) 8X, Selenium Metallicum 8X, Thyroidinum (Suis) 8X, 12X, 30X, 200X, Hepar Bovine 8X, 30X, Hypophysis Suis 8X, 30X, Hypothalamus Suis 8X, 30X, Kidney (Suis) 8X, 30X, Thymus (Suis) 8X, 30X, Levothyroxinum 12C, 30C, 200C, 1M, Triiodothyronine 18C, 30C, 60C, 300C.

INDICATIONS:

For the temporary relief of Fatigue, anxiety, confusion and no energy.

WARNINGS:

If pregnant or breast-feeding, ask a health professional before use.

Keep out of reach of children. In case of overdose, get medical help or contact a Poison Control Center right away.

Do not use if tamper evident seal is broken or missing. Store in a cool, dry place.

Keep out of reach of children. In case of overdose, get medical help or contact a Poison Control Center right away.

DIRECTIONS:

Adults:

Chronic: 5 drops orally 2 times daily, morning and early afternoon, on an empty stomach.

Acute: 5 drops orally 3 or 4 times daily.

Consult a physician for use in children under 12 years of age.

INDICATIONS:

For the temporary relief of Fatigue, anxiety, confusion and no energy.

INACTIVE INGREDIENTS:

Demineralized Water, 25% Organic Ethanol

QUESTIONS:

MFD FOR:

The Wellness Center for Research

and Education, Inc.

1237 S. Victoria Ave. Suite 169

Oxnard, CA 93035

www.wellnesscenter.net

PACKAGE LABEL DISPLAY:

Dr. Theresa Dale's

NDC: 50181-0071-1

Homeopathic

Thyro T3 Rescue

1 fl oz (30 ml)